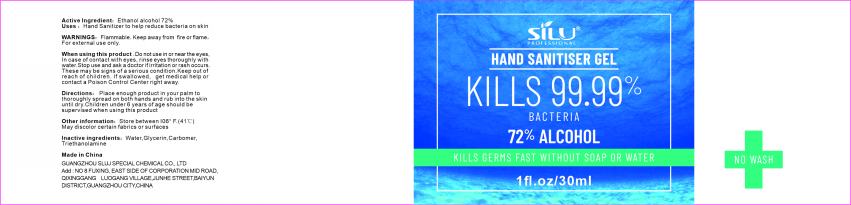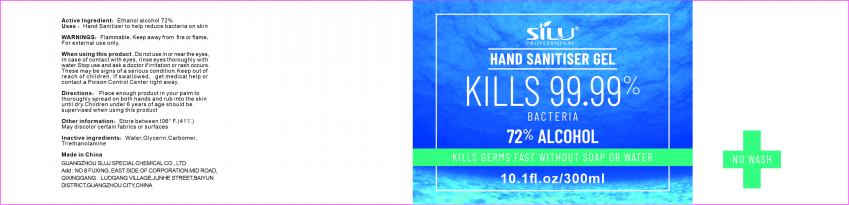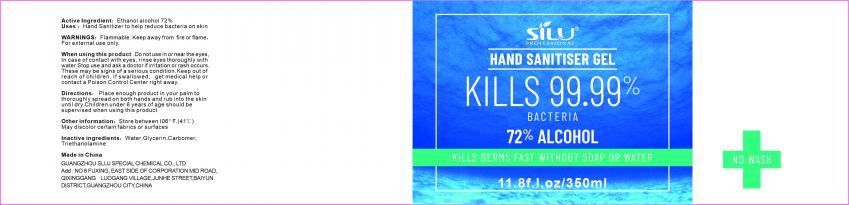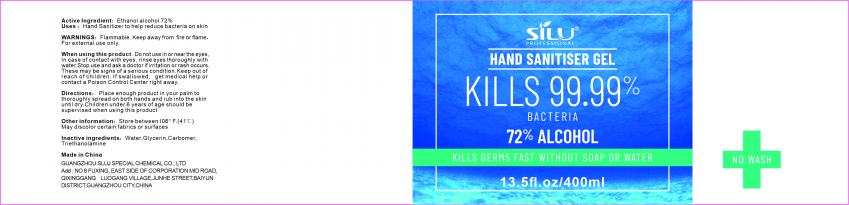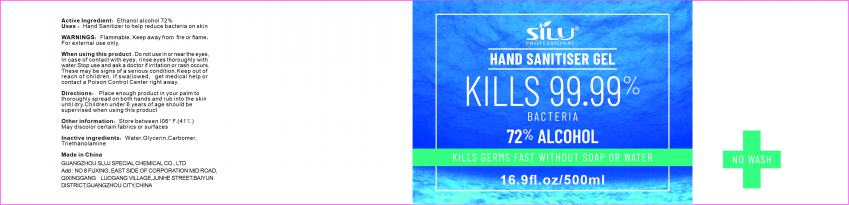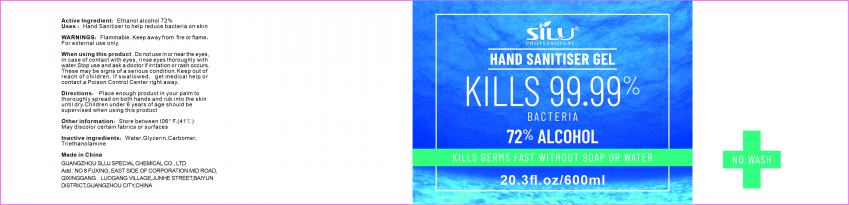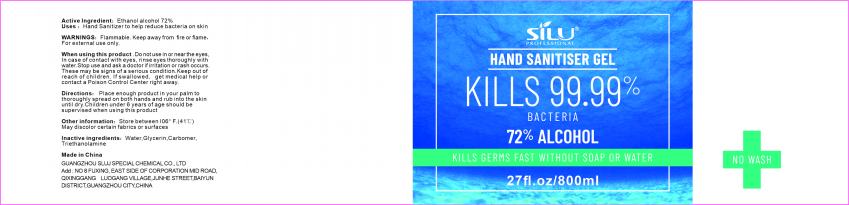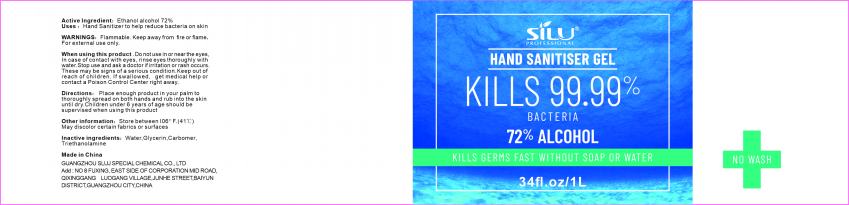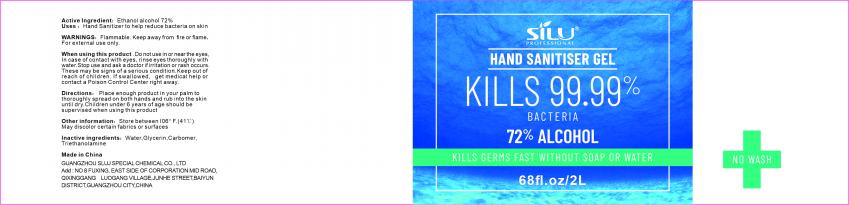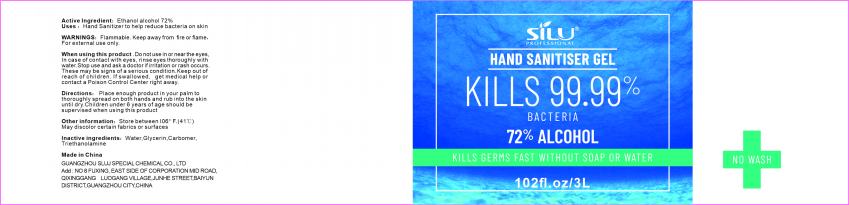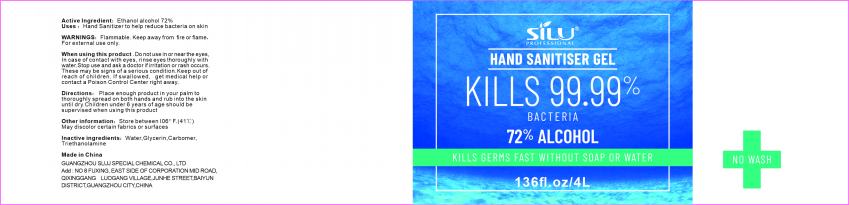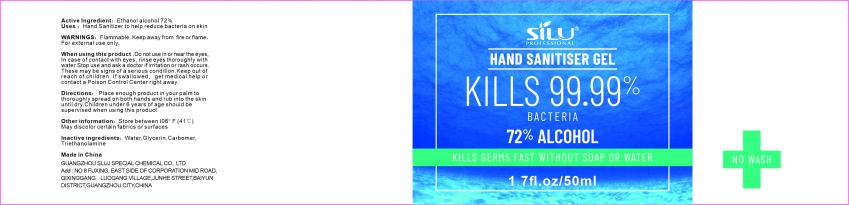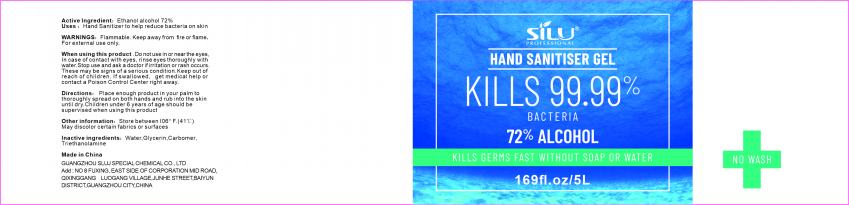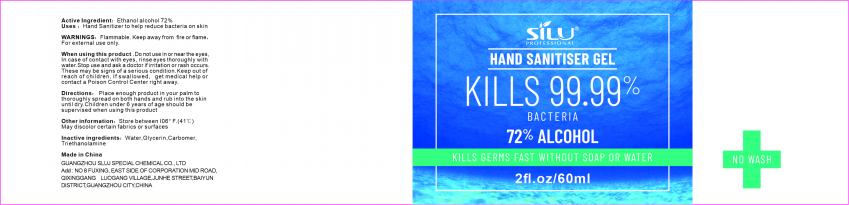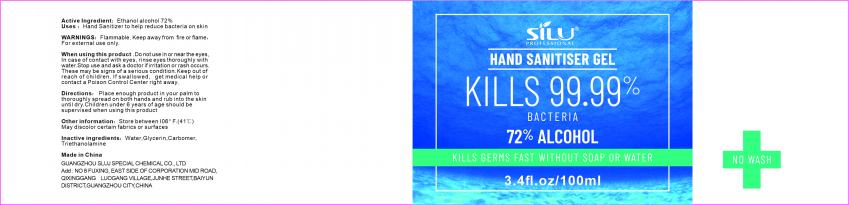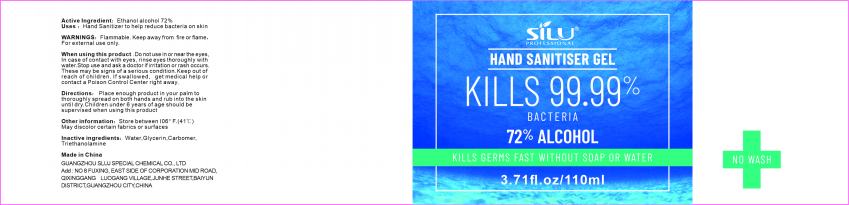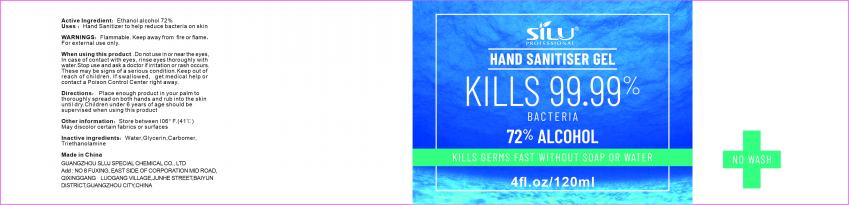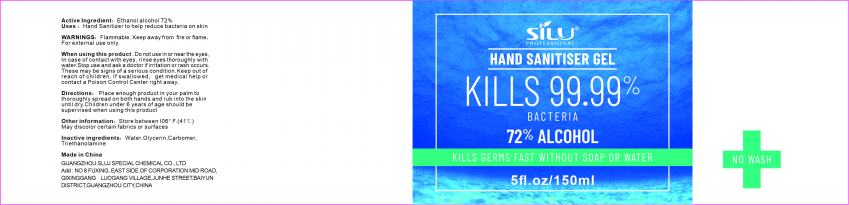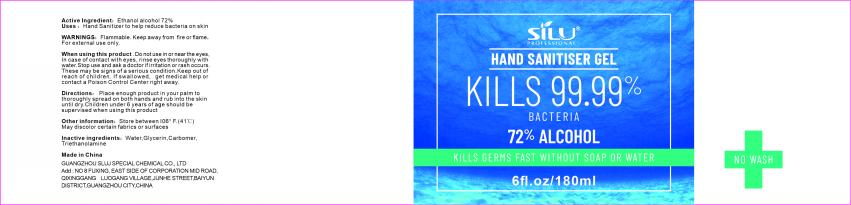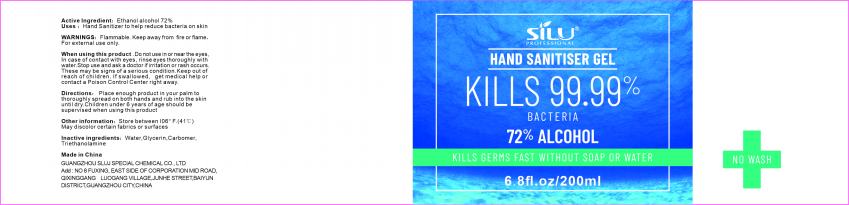 DRUG LABEL: Hand Sanitiser Gel
NDC: 75763-001 | Form: GEL
Manufacturer: GUANGZHOU SLUJ SPECIAL CHEMICAL CO., LTD
Category: otc | Type: HUMAN OTC DRUG LABEL
Date: 20200425

ACTIVE INGREDIENTS: ALCOHOL 72 mL/100 mL
INACTIVE INGREDIENTS: GLYCERIN; CARBOMER HOMOPOLYMER, UNSPECIFIED TYPE; TROLAMINE; WATER

Hand Sanitizer Gel

Active Ingredient

Ethanol alcohol 72%

Uses

Hand Sanitizer to help reduce bacteria on skin

WARNINGS

Flammable.Keep away from fire or flame,For external use only.

When using this product

Do not use in or near the eyes, In case of contact with eyes, rinse eyes thoroughly with water.Stop use and ask a doctor if irritation or rash occurs.These may be signs of a serious condition.Keep out of reach of children.If swallowed, get medical help or contact a Poison Control Center right away.

Directions

Place enough product in your palm to thoroughly spread on both hands and rub into the skin until dry.Children under 6 years of age should be supervised when using this product.

Other information

Store between 106°F.(41℃)

May discolor certain fabrics or surfaces

Inactive ingredients

Water, Glycerin, Carbomer,Triethanolamine